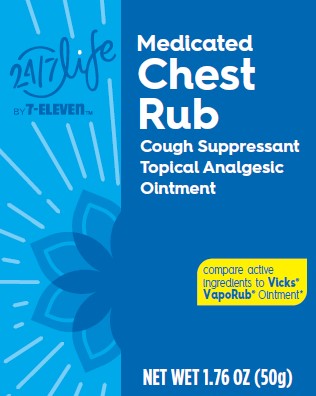 DRUG LABEL: 24/7 Life Medicated Chest Rub
NDC: 29485-6536 | Form: OINTMENT
Manufacturer: Lil' Drug Store Products, Inc.
Category: otc | Type: HUMAN OTC DRUG LABEL
Date: 20250702

ACTIVE INGREDIENTS: EUCALYPTUS OIL 1.2 g/100 g; CAMPHOR (SYNTHETIC) 4.8 g/100 g; MENTHOL 2.6 g/100 g
INACTIVE INGREDIENTS: NUTMEG OIL; PETROLATUM; THYMOL; TURPENTINE OIL; CEDAR LEAF OIL; PARAFFIN

24 / 7 Medicated Chest Rub - (7-Eleven)

Active Ingredients

Camphor 4.8%

Menthol 2.6%

Eucalyptus oil 1.2%

Purpose

Camphor: cough suppressant / topical analgesic

Menthol: cough suppressant / topical analgesic

Eucalyptus oil: cough suppressant

Uses

- Use on chest and throat to temporarily relieve cough associated with the common cold
- Use on muscles to temporarily relieve minor aches and pains of muscles

Warnings

Do not use

- by mouth
- in nostrils
- on wounds or damaged skin
- with tight bandages

Ask a doctor before use if you have

- cough that occurs with too much phlegm (mucus)
- persistent or chronic cough such as occurs with smoking, asthma or emphysema

When using this product, do not

- heat
- microwave
- add to hot water or any container where heating water.

May cause splattering and result in burns.

Stop use and ask a doctor if

- muscle aches and pains worsen or persist for more than 7 days or clear up and occur again within a few days.
- cough persists for more than 1 week, tends to recur, or is accompanied by fever, rash, or persistent headache. A persistent cough may be a sign of a serious condition.

If pregnant or breast feeding,

ask a health professional before use.

Keep out of reach of children.

If swallowed, get medical help or contact a Poison Control Center right away.

Directions

see important warnings under “When using this product”

- adults and children 2 years and over:
- for cough suppression
- rub a thick layer on throat & chest
- cover with a warm, dry cloth if desired
- keep clothing loose about throat and chest to help vapors reach the nose and mouth
- use up to three times daily or as directed by doctor
- for muscle/joint minor aches and pains apply to affected area not more than 3 to 4 times daily
- children under 2 years: do not use

Other Information

- store at 59°-86°F (15°-30°C)

Inactive Ingredients

cedar leaf oil, nutmeg oil, paraffin, petrolatum, thymol, turpentine oil

Questions or comments?

1-800-351-2000 (8:00 AM – 4:30 PM CST)

*This product is not manufactured or distributed by The Procter & Gamble Company. Vicks® and VapoRub®

are registered trademarks of the Procter & Gamble Company.

Satisfaction Guaranteed 1-800-255-0711

Distributed by:

7-Eleven, Inc. Irving, TX 75063

www.7-ELEVEN.com

Made in India

1.76oz Jar

24/7 Life by 7-ELEVEN

Medicated

Chest

Rub

Cough Suppressant

Topical Analgesic

Ointment

Compare Active Ingredients to VICKS®

VapoRub® Ointment*

NET WT 1.76 OZ (50g)